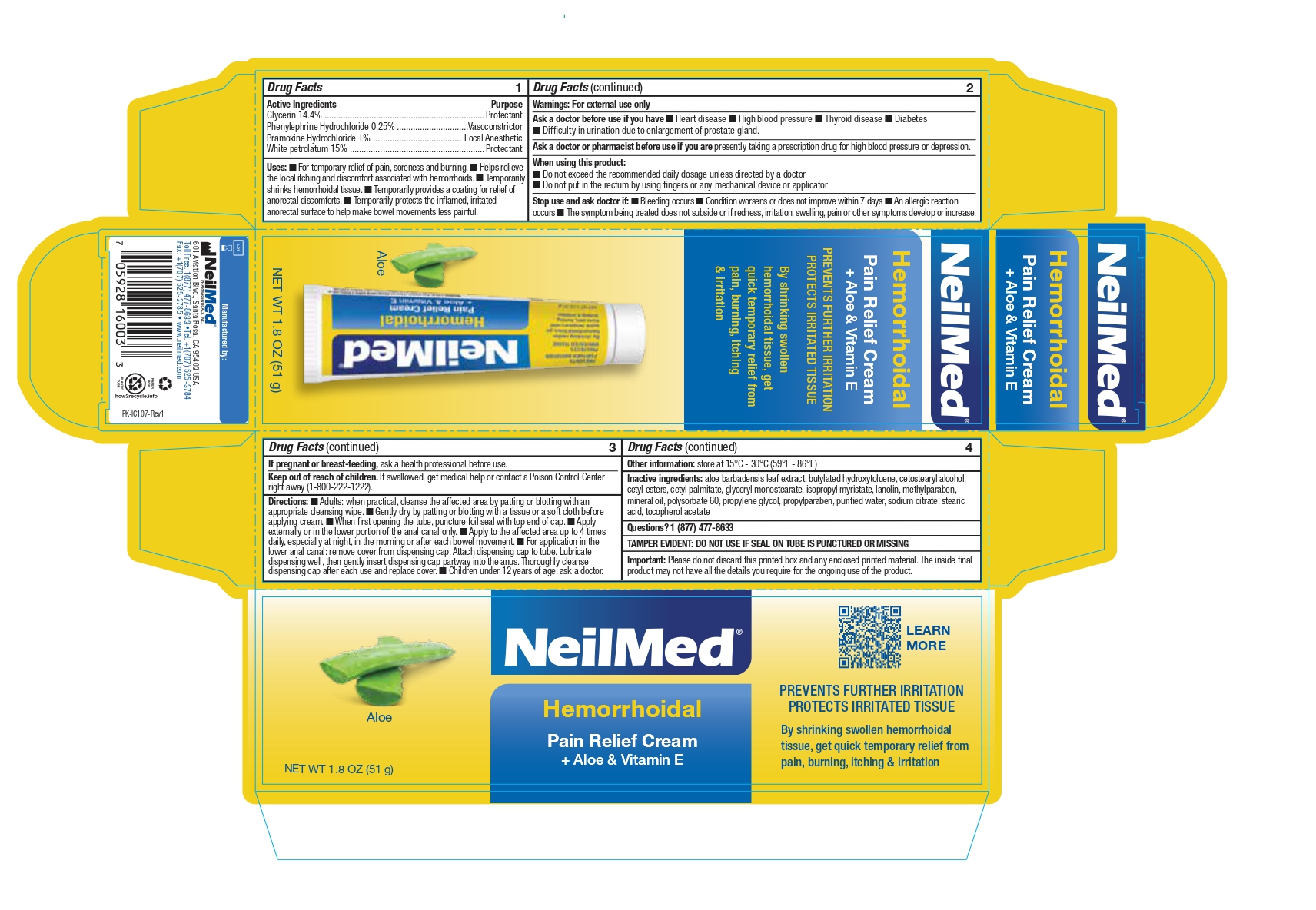 DRUG LABEL: Hemorrhoidal Pain Relief with Aloe and VitaminE
NDC: 13709-324 | Form: CREAM
Manufacturer: NeilMed pharmaceuticals Inc.
Category: otc | Type: HUMAN OTC DRUG LABEL
Date: 20231011

ACTIVE INGREDIENTS: PHENYLEPHRINE HYDROCHLORIDE 25 mg/1 g; PETROLATUM 150 mg/1 g; PRAMOXINE HYDROCHLORIDE 10 mg/1 g; GLYCERIN 144 mg/1 g
INACTIVE INGREDIENTS: PROPYLENE GLYCOL; SODIUM CITRATE; STEARIC ACID; WATER; MINERAL OIL; CETYL PALMITATE; LANOLIN; METHYLPARABEN; BUTYLATED HYDROXYTOLUENE; CETOSTEARYL ALCOHOL; ISOPROPYL MYRISTATE; GLYCERYL MONOSTEARATE; PROPYLPARABEN; ALOE; POLYSORBATE 60; CETYL ESTERS WAX; .ALPHA.-TOCOPHEROL ACETATE

Hemorrhoidal Pain Relief Cream with Aloe and Vitamin E

Drug Facts - Active Ingredients

Glycerin 14.4%
Phenylephrine Hydrochloride 0.25%
Pramoxine Hydrochloride 1%
White petrolatum 15%

Purpose

Glycerin 14.4% ..................................................................... Protectant
Phenylephrine Hydrochloride 0.25% ...............................Vasoconstrictor
Pramoxine Hydrochloride 1% ...................................... Local Anesthetic
White petrolatum 15% .......................................................... Protectant

Uses:

􀁑􀀃For temporary relief of pain, soreness and burning. 􀁑􀀃Helps relieve the local itching and discomfort associated with hemorrhoids. 􀁑􀀃Temporarily shrinks hemorrhoidal tissue. 􀁑􀀃Temporarily provides a coating for relief of anorectal discomforts. 􀁑􀀃Temporarily protects the inflamed, irritated anorectal surface to help make bowel movements less painful.

Warnings:

For external use only

Ask a doctor before use if you have

􀁑􀀃Heart disease 􀁑􀀃High blood pressure 􀁑􀀃Thyroid disease 􀁑􀀃Diabetes􀁑􀀃Difficulty in urination due to enlargement of prostate gland.

Ask a doctor or pharmacist before use

if you are presently taking a prescription drug for high blood pressure or depression.

When using this product:

􀁑􀀃Do not exceed the recommended daily dosage unless directed by a doctor
􀁑􀀃Do not put in the rectum by using fingers or any mechanical device or applicator

Stop use and ask doctor if:

􀁑􀀃Bleeding occurs 􀁑􀀃Condition worsens or does not improve within 7 days 􀁑􀀃An allergic reaction occurs 􀁑􀀃The symptom being treated does not subside or if redness, irritation, swelling, pain or other symptoms develop or increase.

If pregnant or breast-feeding, ask a health professional before use.

Keep out of reach of children

If swallowed, get medical help or contact a Poison Control Center right away (1-800-222-1222).

Directions:

􀁑􀀃Adults: when practical, cleanse the affected area by patting or blotting with an appropriate cleansing wipe. 􀁑􀀃Gently dry by patting or blotting with a tissue or a soft cloth before applying cream. 􀁑􀀃When first opening the tube, puncture foil seal with top end of cap. 􀁑􀀃Apply externally or in the lower portion of the anal canal only. 􀁑􀀃Apply to the affected area up to 4 times daily, especially at night, in the morning or after each bowel movement. 􀁑􀀃For application in the lower anal canal: remove cover from dispensing cap. Attach dispensing cap to tube. Lubricate dispensing well, then gently insert dispensing cap partway into the anus. Thoroughly cleanse
dispensing cap after each use and replace cover. 􀁑􀀃Children under 12 years of age: ask a doctor.

Inactive ingredients:

aloe barbadensis leaf extract, butylated hydroxytoluene, cetostearyl alcohol, cetyl esters, cetyl palmitate, glyceryl monostearate, isopropyl myristate, lanolin, methylparaben, mineral oil, polysorbate 60, propylene glycol, propylparaben, purified water, sodium citrate, stearic acid, tocopherol acetate

Questions?

Questions? 1 (877) 477-8633

TAMPER EVIDENT:

TAMPER EVIDENT: DO NOT USE IF SEAL ON TUBE IS PUNCTURED OR MISSING

Important

Important: Please do not discard this printed box and any enclosed printed material. The inside final product may not have all the details you require for the ongoing use of the product.

Use

swollen hemorrhoidal tissue, to get quick temporary relief from pain, burning, itching& irritation